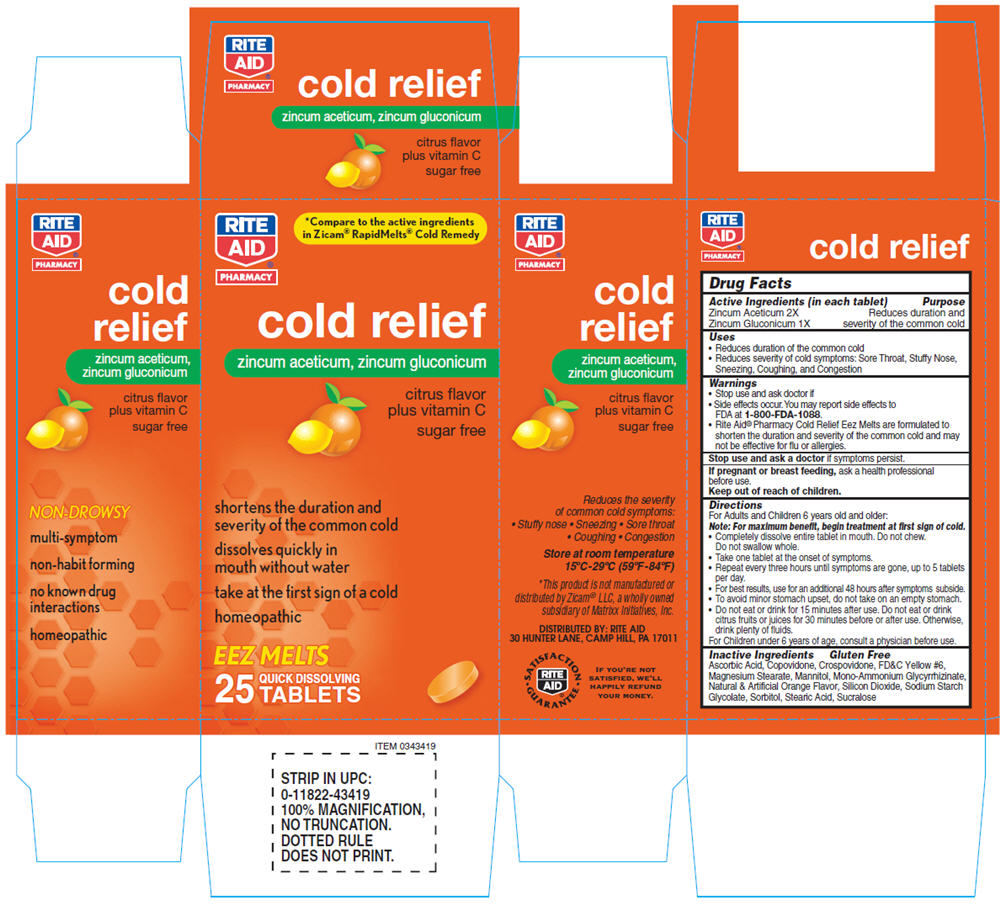 DRUG LABEL: NBE Citrus 
NDC: 64762-873 | Form: TABLET, ORALLY DISINTEGRATING
Manufacturer: Dynamic Pharmaceuticals Inc.
Category: homeopathic | Type: HUMAN OTC DRUG LABEL
Date: 20100924

ACTIVE INGREDIENTS: Zinc Acetate 2 [hp_X]/1 1; Zinc Gluconate 1 [hp_X]/1 1
INACTIVE INGREDIENTS: Ascorbic Acid; Copovidone; Crospovidone; FD&C Yellow NO. 6; Magnesium Stearate; Mannitol; GLYCYRRHIZIN, AMMONIATED; Silicon Dioxide; SODIUM STARCH GLYCOLATE TYPE A POTATO; Sorbitol; Stearic Acid; Sucralose

RITE
AID®
PHARMACY

Drug Facts

ACTIVE INGREDIENT

Active Ingredients (in each tablet) | Purpose
Zincum Aceticum 2X | Reduces duration and
Zincum Gluconicum 1X | severity of the common cold

Uses

- Reduces duration of the common cold
- Reduces severity of cold symptoms: Sore Throat, Stuffy Nose, Sneezing, Coughing, and Congestion

Warnings

- Stop use and ask doctor if
- Side effects occur. You may report side effects to FDA at 1-800-FDA-1088.
- Rite Aid® Pharmacy Cold Relief Eez Melts are formulated to shorten the duration and severity of the common cold and may not be effective for flu or allergies.

Stop use and ask a doctor if symptoms persist.

PREGNANCY OR BREAST FEEDING

If pregnant or breast feeding, ask a health professional before use.

Keep out of reach of children.

Directions

For Adults and Children 6 years old and older:
Note: For maximum benefit, begin treatment at first sign of cold.

- Completely dissolve entire tablet in mouth. Do not chew.
  Do not swallow whole.
- Take one tablet at the onset of symptoms.
- Repeat every three hours until symptoms are gone, up to 5 tablets per day.
- For best results, use for an additional 48 hours after symptoms subside.
- To avoid minor stomach upset, do not take on an empty stomach.
- Do not eat or drink for 15 minutes after use. Do not eat or drink citrus fruits or juices for 30 minutes before or after use. Otherwise, drink plenty of fluids.

For Children under 6 years of age, consult a physician before use.

Inactive Ingredients

Gluten Free

Ascorbic Acid, Copovidone, Crospovidone, FD&C Yellow #6, Magnesium Stearate, Mannitol, Mono-Ammonium Glycyrrhizinate, Natural & Artificial Orange Flavor, Silicon Dioxide, Sodium Starch Glycolate, Sorbitol, Stearic Acid, Sucralose

DISTRIBUTED BY: RITE AID
30 HUNTER LANE, CAMP HILL, PA 17011

PRINCIPAL DISPLAY PANEL - 25 tablet carton

RITE
AID®
PHARMACY

*Compare to the active ingredients
in Zicam® RapidMelts® Cold Remedy

cold relief
zincum aceticum, zincum gluconicum

citrus flavor
plus vitamin C

sugar free

shortens the duration and
severity of the common cold

dissolves quickly in
mouth without water

take at the first sign of a cold

homeopathic

EEZ MELTS

25
QUICK DISSOLVING
TABLETS